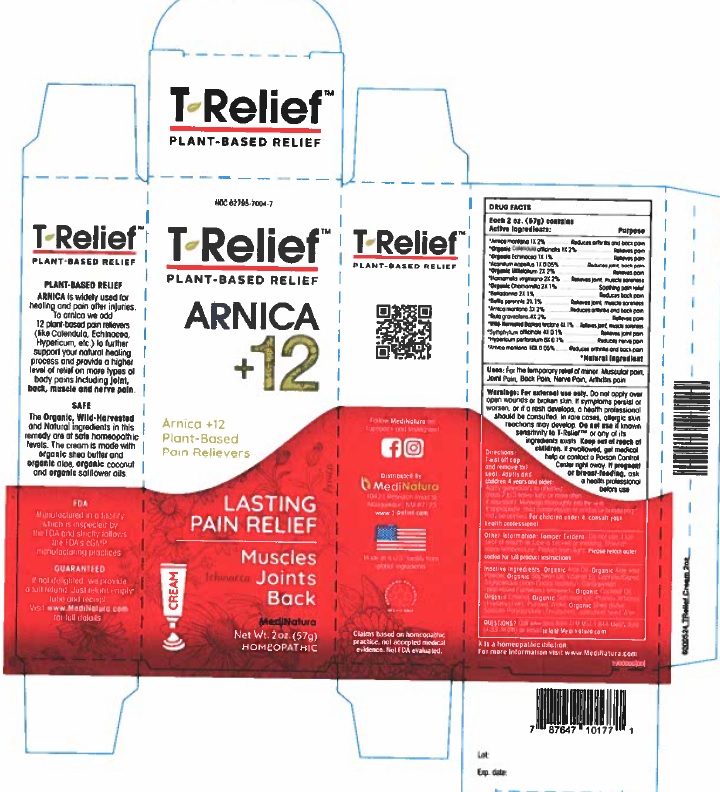 DRUG LABEL: T-Relief
NDC: 62795-7004 | Form: OINTMENT
Manufacturer: MediNatura Inc
Category: homeopathic | Type: HUMAN OTC DRUG LABEL
Date: 20230927

ACTIVE INGREDIENTS: ARNICA MONTANA 1 [hp_X]/1 g; BAPTISIA TINCTORIA ROOT 4 [hp_X]/1 g; ATROPA BELLADONNA 2 [hp_X]/1 g; BELLIS PERENNIS 2 [hp_X]/1 g; CALENDULA OFFICINALIS FLOWERING TOP 1 [hp_X]/1 g; MATRICARIA RECUTITA 2 [hp_X]/1 g; ECHINACEA, UNSPECIFIED 1 [hp_X]/1 g; HAMAMELIS VIRGINIANA ROOT BARK/STEM BARK 2 [hp_X]/1 g; HYPERICUM PERFORATUM 6 [hp_X]/1 g; RUTA GRAVEOLENS FLOWERING TOP 4 [hp_X]/1 g; ACONITUM NAPELLUS 1 [hp_X]/1 g; COMFREY ROOT 4 [hp_X]/1 g; ACHILLEA MILLEFOLIUM 2 [hp_X]/1 g
INACTIVE INGREDIENTS: WATER; SHEA BUTTER; SODIUM POLYACRYLATE (2500000 MW); HELIANTHUS ANNUUS SEED WAX; ALOE; MEDIUM-CHAIN TRIGLYCERIDES; ALCOHOL; SAFFLOWER OIL; PHENOXYETHANOL; CARRAGEENAN; COCONUT OIL

T-Relief Cream

USES

For the temporary relief of minor: Joint Pain • Back Pain • Muscular Pain

KEEP OUT OF REACH OF CHILDREN

INDICATION AND USES

Relieves:

• Joint Pain

• Back Pain

• Muscular Pain

WARNINGS

Warnings: For external use only. Do not apply over open wounds or broken skin. If symptoms persist or worsen, or if a rash develops, a health professional should be consulted. In rare cases, allergic skin reactions may develop. Do not use if known sensitivity to T-ReliefTM or any of its ingredients exists.

Keep out of reach of children. If swallowed, get medical help or contact a Poison Control Center right away. If pregnant or breast-feeding, ask a health professional before use.

INACTIVES INGREDIENTS

Inactive Ingredients: Organic Aloe Oil (Organic Aloe vera Powder, Organic Soybean Oil, Vitamin E), Caprylic/Capric Triglycerides (from Cocos nucifera), Carrageenan (processed Eucheuma seaweed), Organic Coconut Oil, Ethanol (from Organic Cane), Organic Safflower Oil, Phenoxyethanol (Preservative),

Purified Water, Natural Shea Butter, Sodium Polyacrylate

(Emulsifier), Natural Sunflower Seed Wax